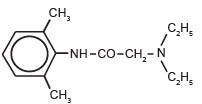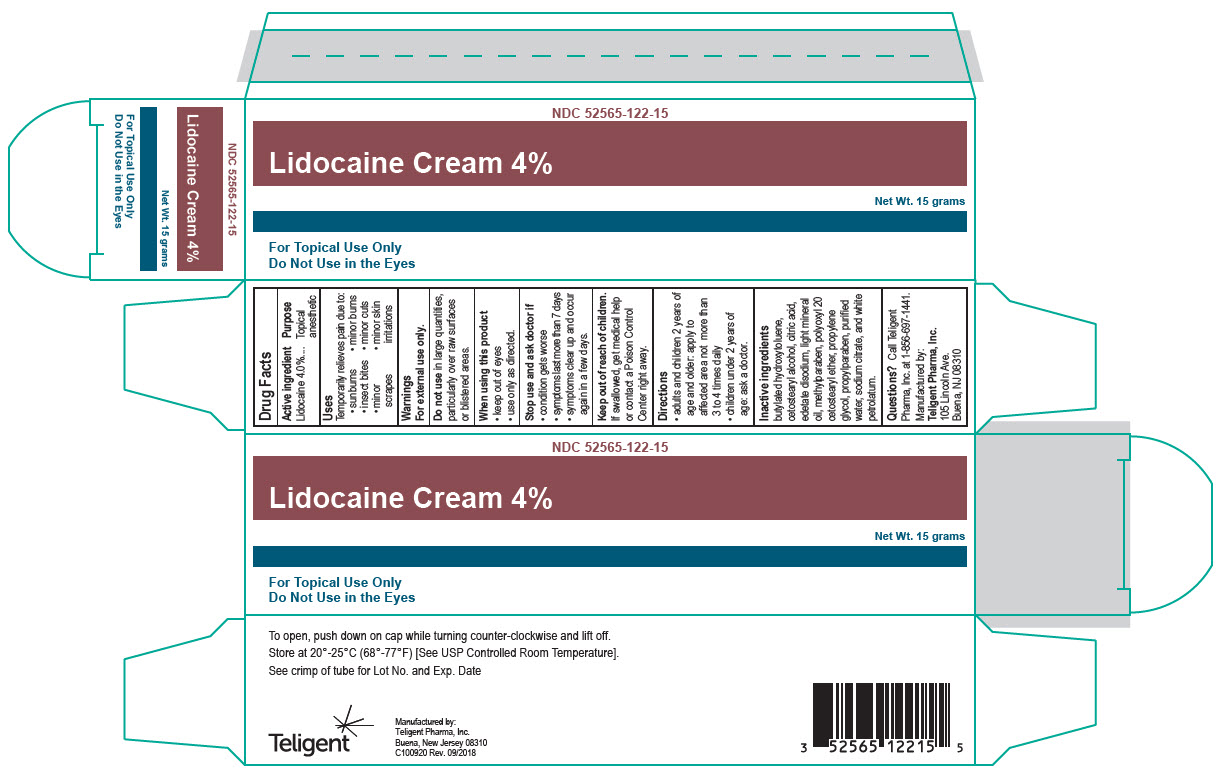 DRUG LABEL: Lidocaine 4% Cream
NDC: 52565-122 | Form: CREAM
Manufacturer: Teligent Pharma, Inc.
Category: otc | Type: HUMAN OTC DRUG LABEL
Date: 20190122

ACTIVE INGREDIENTS: LIDOCAINE 4 g/100 g
INACTIVE INGREDIENTS: Butylated Hydroxytoluene; Cetostearyl Alcohol; Citric Acid Acetate; Edetate Disodium Anhydrous; Light Mineral Oil; Methylparaben; Polyoxyl 20 Cetostearyl Ether; Propylparaben; Water; Sodium Citrate, Unspecified Form; Petrolatum; Propylene Glycol

Lidocaine 4% Cream

DESCRIPTION

Lidocaine 4% cream is a non-greasy cream specially formulated with soothing agents, indicated as a topical anesthetic for use on normal intact skin for local analgesia and itching due to minor cuts, minor scrapes, sunburn, minor skin irritations, minor burns and insect bites.

INGREDIENTS

ACTIVE: Lidocaine (4%)

INACTIVE:

Butylated Hydroxytoluene, Cetostearyl Alcohol, Citric Acid, Edetate Disodium, Light Mineral Oil, Methylparaben, Polyoxyl 20 Cetostearyl Ether, Propylene Glycol, Propylparaben, Purified Water, Sodium Citrate and White Petrolatum.

The chemical designation of Lidocaine is 2-(diethylamino)-N(2,6-dimethylphenyl), acetamide. The structure of lidocaine is:

MECHANISM OF ACTION

Lidocaine 4% cream applied to intact skin provides dermal analgesia by the release of lidocaine from the cream into the epidermis and dermis. Lidocaine is a local anesthetic agent of the amide type. Local anesthetics reversibly block the initiation and conduction of nerve impulses by interfering with the flux of sodium ions through the neuronal membrane. The onset, depth and duration of dermal analgesia provided depend upon the site and duration of application.

INDICATIONS AND USAGE

Lidocaine 4% cream is indicated for use on normal intact skin for temporary relief of pain and itching due to minor cuts, minor scrapes, minor skin irritations, minor burns and insect bites.
Lidocaine 4% cream is not recommended for internal use, in the or near the eyes and in large quantities, particularly over raw surfaces or blistered areas.

CONTRAINDICATIONS

Lidocaine 4% cream is contraindicated in patients with sensitivity to amide type local anesthetics or to any component of the product.

WARNINGS

For external use only. Avoid contact with the eyes. Do not use over large areas of the body. Do not use for more than seven days unless directed by a doctor. Keep this and all drugs out of the reach of children. In case of accidental ingestion, seek professional assistance or contact a Poison Control Center immediately.
Inappropriate use of this product, such as on large areas of the body, application on mucous membranes, or on individuals that are allergic to the amide type anesthetics, may result in serious side effects. Consultation with a doctor before using this product is strongly recommended.

PRECAUTIONS

Repeated doses of lidocaine 4% cream may increase blood levels of lidocaine. Avoid contact with the eyes. If eye contact occurs, immediately wash out the eye with water or saline.
The patient should be aware that dermal analgesia may be accompanied by the block of all sensations in the treated skin. For this reason, the patient should avoid inadvertent trauma to the treated area by scratching, rubbing or exposure to extreme hot or cold temperatures until complete sensation has returned.

DRUG INTERACTIONS

Lidocaine 4% cream should be used with caution in patients receiving Class I antiarrhythmic agents (e.g., tocainide, mexiletine) since the toxic effects are potentially additive and synergistic.

- Adults and children 2 years and older. Apply externally to the affected area up to 3 to 4 times a day.
- Children under 2 years of age. Consult a doctor.

HOW SUPPLIED

NDC 52565-122-07 (5 x 5 gram tubes)
NDC 52565-122-15 (15 gram tubes)
NDC 52565-122-30 (30 gram tubes)
Store at USP controlled room temperature 20° to 25°C (68° to 77°F).
Manufactured by:
Teligent Pharma, Inc.
Buena, New Jersey 08310
PI-122-01
Revised 09/2018

PACKAGE LABEL.PRINCIPAL DISPLAY PANEL

NDC 52565-122-15
Lidocaine Cream 4%
Net Wt. 15 grams
For Topical Use Only
Do Not Use in the Eyes